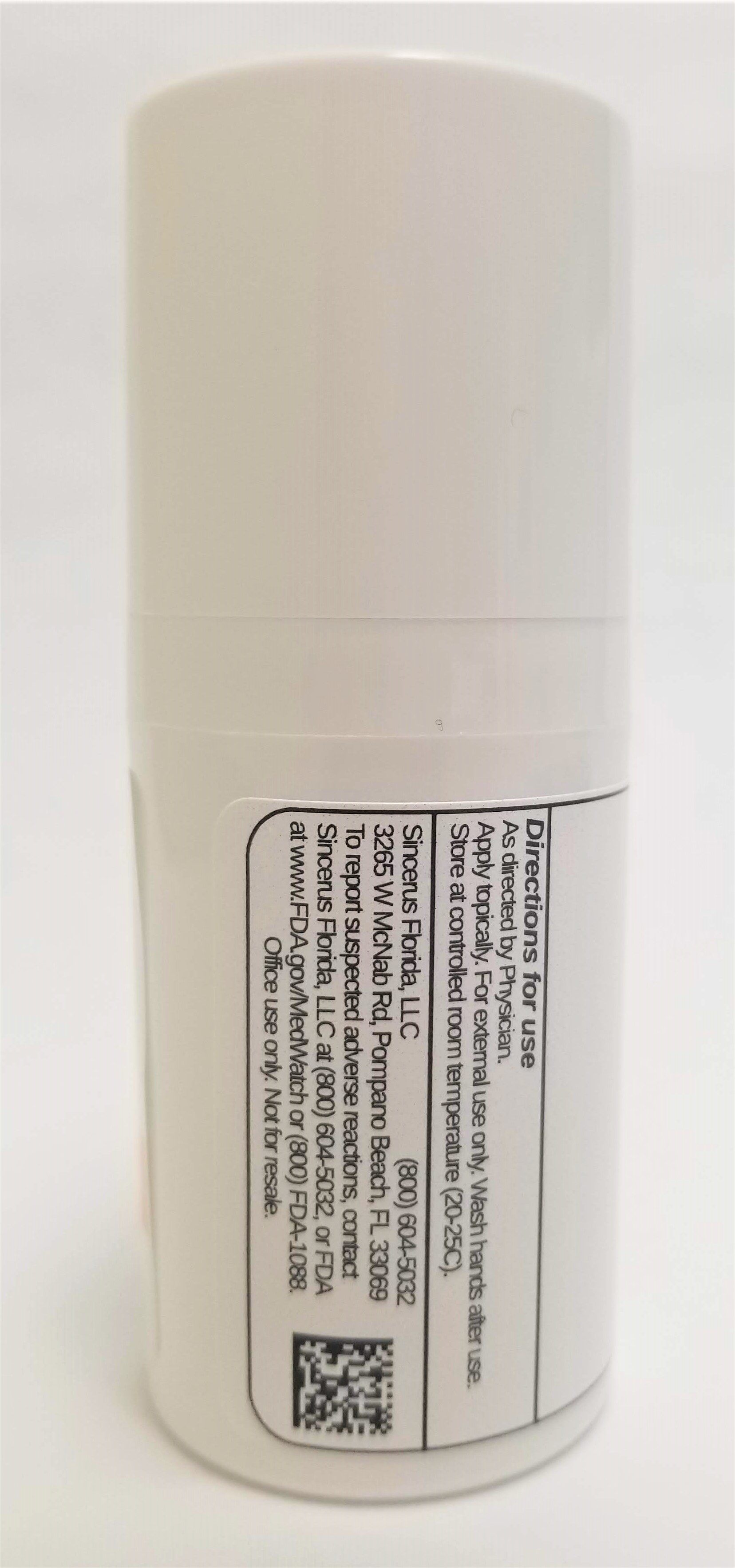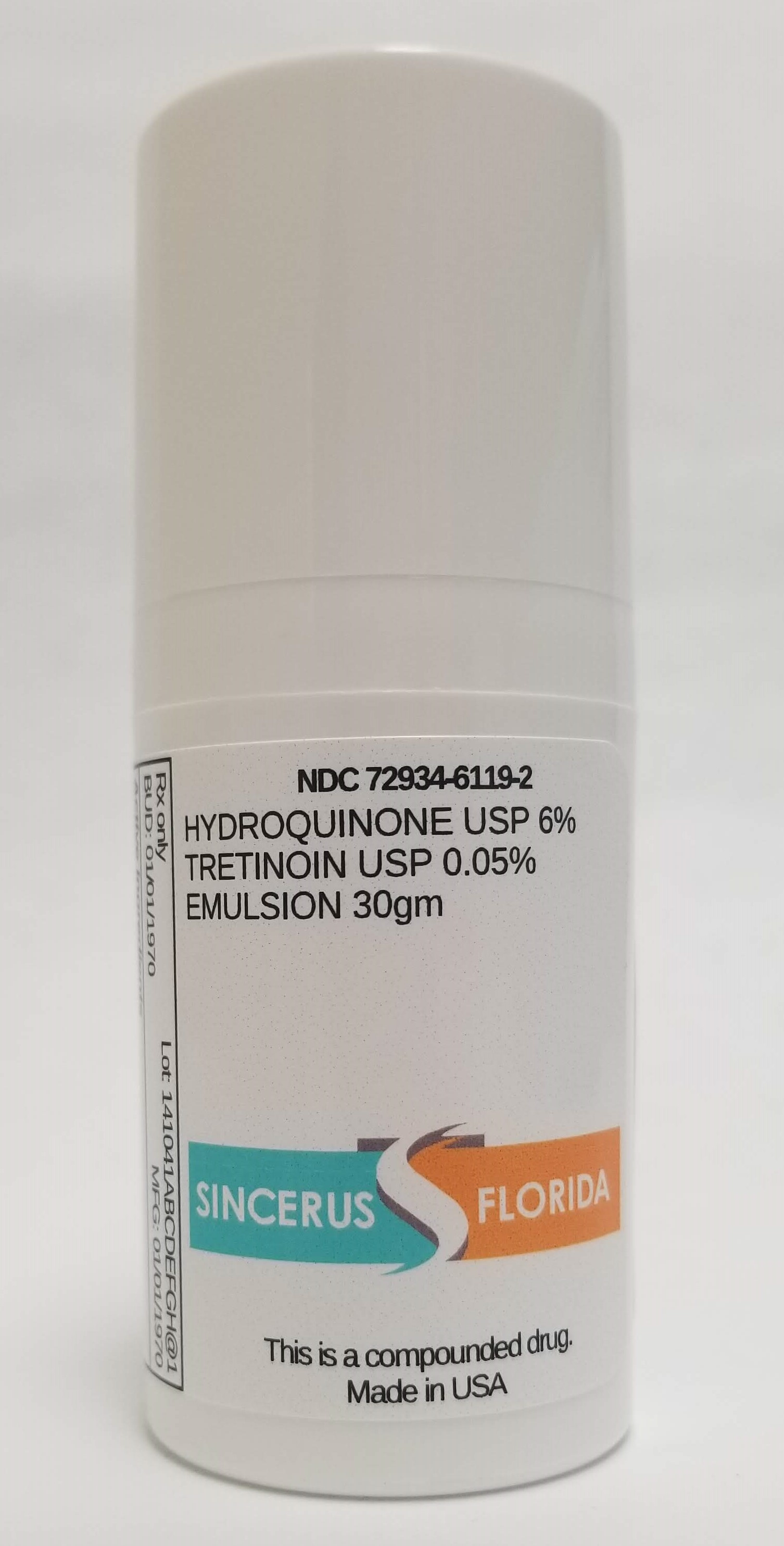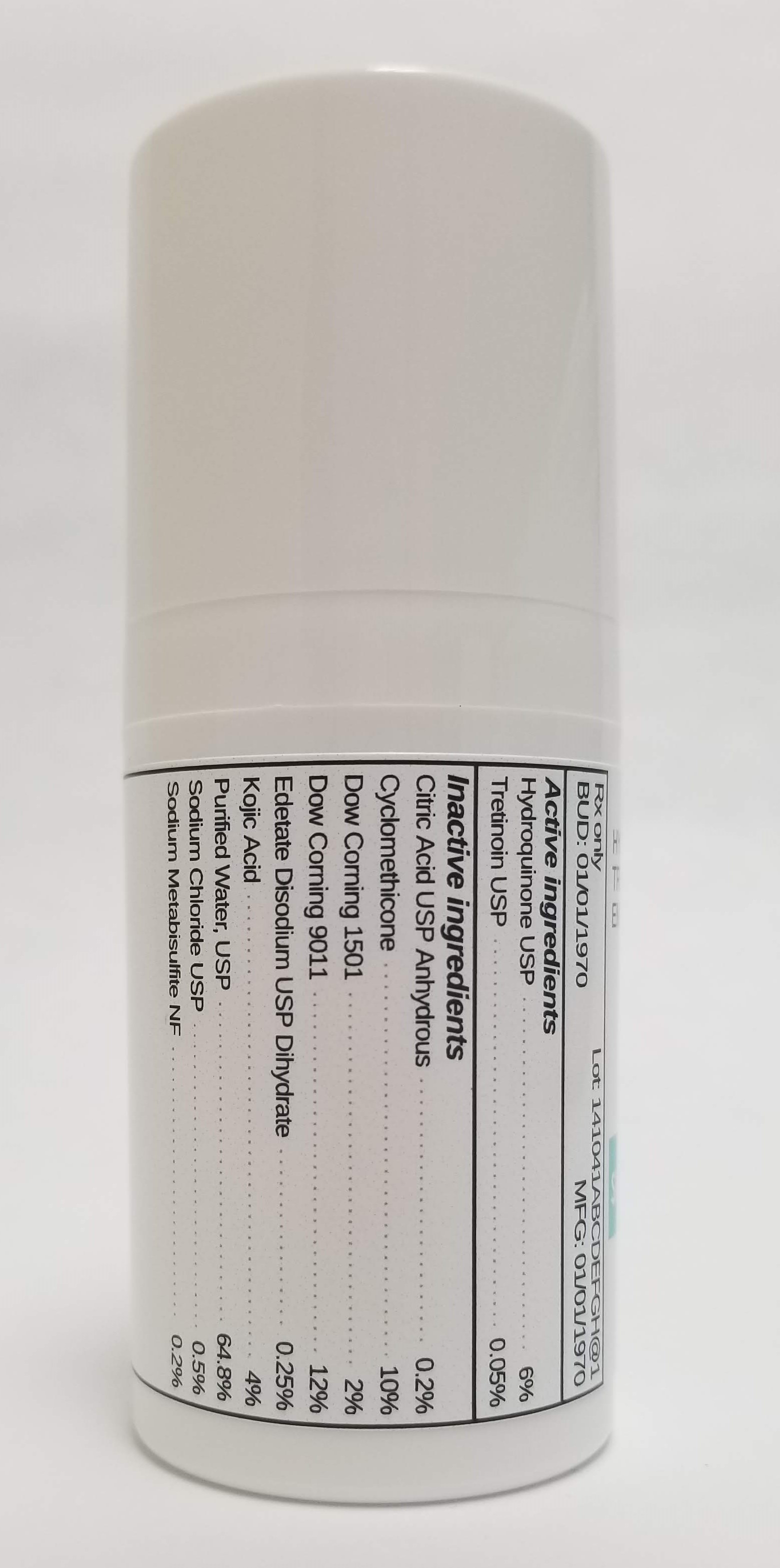 DRUG LABEL: HYDROQUINONE 6% /TRETINOIN 0.05%
NDC: 72934-6119 | Form: EMULSION
Manufacturer: Sincerus Florida, LLC
Category: prescription | Type: HUMAN PRESCRIPTION DRUG LABEL
Date: 20190520

ACTIVE INGREDIENTS: HYDROQUINONE 6 g/100 g; TRETINOIN 0.05 g/100 g

HYDROQUINONE 6% /TRETINOIN 0.05%